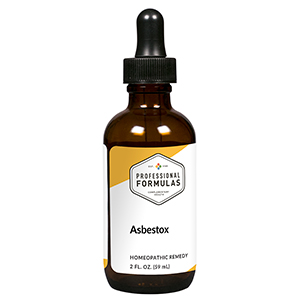 DRUG LABEL: Asbestox
NDC: 63083-6005 | Form: LIQUID
Manufacturer: Professional Complementary Health Formulas
Category: homeopathic | Type: HUMAN OTC DRUG LABEL
Date: 20190815

ACTIVE INGREDIENTS: SELENICEREUS GRANDIFLORUS STEM 6 [hp_X]/59 mL; IRON 6 [hp_X]/59 mL; BEEF LUNG 6 [hp_X]/59 mL; IODINE 12 [hp_X]/59 mL; FERULA ASSA-FOETIDA RESIN 12 [hp_X]/59 mL; MOSCHUS MOSCHIFERUS MUSK SAC RESIN 12 [hp_X]/59 mL; PHOSPHORUS 12 [hp_X]/59 mL; SULFUR 12 [hp_X]/59 mL; SILICON DIOXIDE 12 [hp_X]/59 mL; AMOSITE 30 [hp_X]/59 mL
INACTIVE INGREDIENTS: ALCOHOL; WATER

X5

ACTIVE INGREDIENTS

Cactus grandiflorus 6X
Ferrum metallicum 6X
Lung 6X, 12X, 30X
Iodium 12X
Asafoetida 12X, 30X
Moschus 12X, 30X
Phosphorus 12X, 30X
Sulphur 12X, 30X
Silicea 12X, 30X, 60X
Asbestos 30X, 60X, 100X

QUESTIONS

Professional Formulas

PO Box 2034 Lake Oswego, OR 97035

INDICATIONS

For the temporary relief of cough, shortness of breath, loss of appetite, nausea, or fatigue due to sensitivity to or exposure to environments that previously contained asbestos.*

PURPOSE

*Claims based on traditional homeopathic practice, not accepted medical evidence. Not FDA evaluated.

WARNINGS

Consult a doctor if condition worsens or symptoms persist. Keep out of the reach of children. In case of overdose, get medical help or contact a poison control center right away. If pregnant or breastfeeding, ask a healthcare professional before use.

Keep out of the reach of children.

PREGNANCY OR BREAST FEEDING

If pregnant or breastfeeding, ask a healthcare professional before use.

DIRECTIONS

Place drops under tongue 30 minutes before/after meals. Adults and children 12 years and over: Take 10 drops up to 3 times per day. Consult a physician for use in children under 12 years of age.

OTHER INFORMATION

Tamper resistant. If seal is broken, do not use. After opening, close container tightly and store at room temperature away from heat.

INACTIVE INGREDIENTS

20% ethanol, purified water.

LABEL

Est 1985

Professional Formulas

Complementary Health

Asbestox

Homeopathic Remedy

2 FL. OZ. (59 mL)